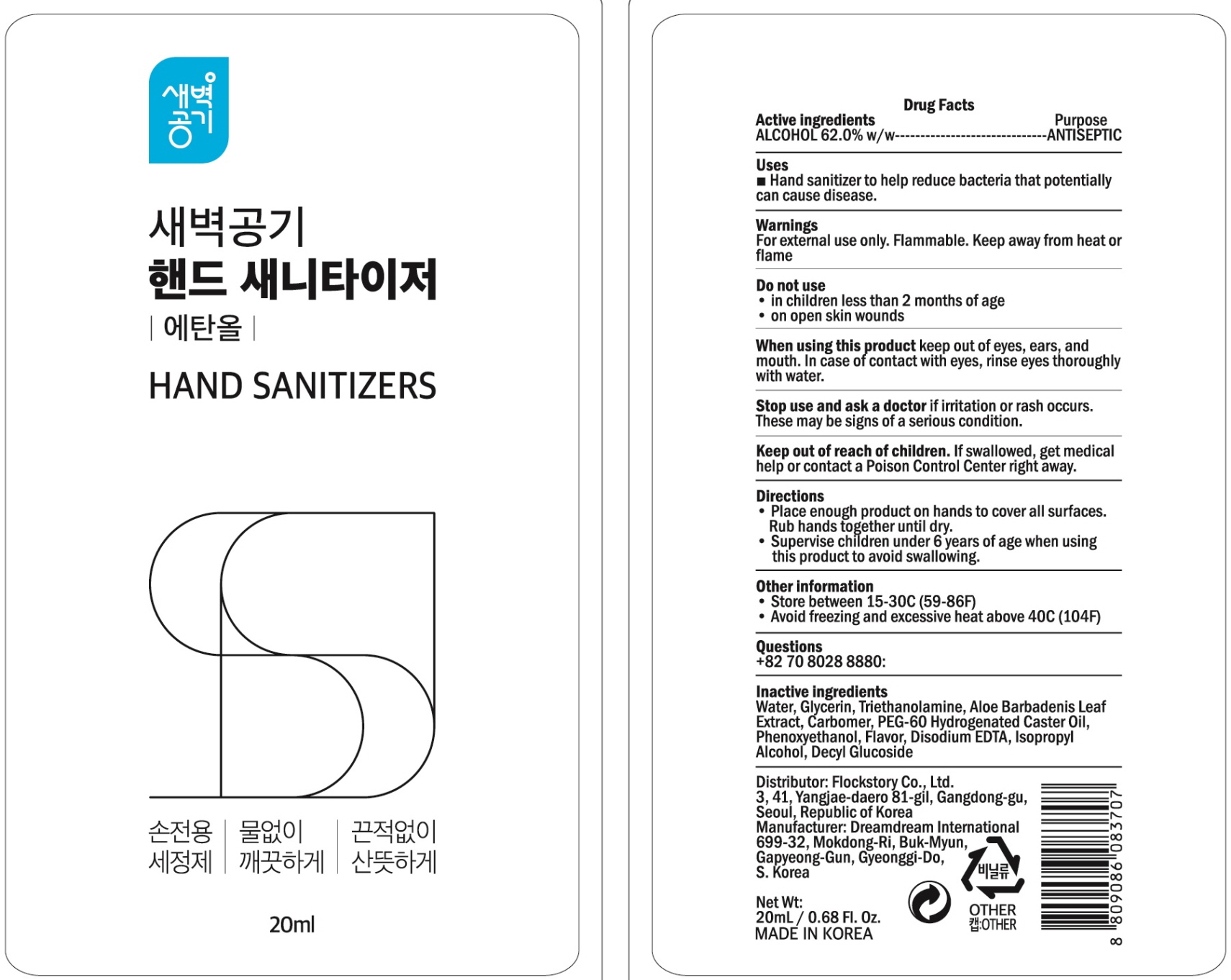 DRUG LABEL: Sebyuk Gonggi Hand Sanitizers
NDC: 74779-020 | Form: GEL
Manufacturer: Flockstory Co., Ltd.
Category: otc | Type: HUMAN OTC DRUG LABEL
Date: 20200427

ACTIVE INGREDIENTS: ALCOHOL 12.4 g/20 mL
INACTIVE INGREDIENTS: Water; Glycerin; TROLAMINE; ALOE VERA LEAF; CARBOMER HOMOPOLYMER, UNSPECIFIED TYPE; PEG-60 Hydrogenated Castor Oil; Phenoxyethanol; EDETATE DISODIUM ANHYDROUS; Isopropyl Alcohol; Decyl Glucoside

ACTIVE INGREDIENT

Active ingredients: ALCOHOL 62.0% w/w

INACTIVE INGREDIENT

Inactive Ingredients:

Water, Glycerin, Triethanolamine, Aloe Barbadenis Leaf Extract, Carbomer, PEG-60 Hydrogenated Caster Oil, Phenoxyethanol, Flavor, Disodium EDTA, Isopropyl Alcohol, Decyl Glucoside

PURPOSE

Purpose: ANTISEPTIC

WARNINGS

For external use only. Flammable. Keep away from heat or flame
--------------------------------------------------------------------------------------------------------
Do not use
• in children less than 2 months of age
• on open skin wounds
--------------------------------------------------------------------------------------------------------
When using this product keep out of eyes, ears, and mouth. In case of contact with eyes, rinse eyes thoroughly with water.
--------------------------------------------------------------------------------------------------------
Stop use and ask a doctor if irritation or rash occurs. These may be signs of a serious condition.

Keep out of reach of children. If swallowed, get medical help or contact a Poison Control Center right away.

Uses

■ Hand sanitizer to help reduce bacteria that potentially can cause disease.

Directions

• Place enough product on hands to cover all surfaces. Rub hands together until dry.
• Supervise children under 6 years of age when using this product to avoid swallowing.

Other Information

• Store between 15-30C (59-86F)
• Avoid freezing and excessive heat above 40C (104F)

QUESTIONS

+82 70 8028 8880